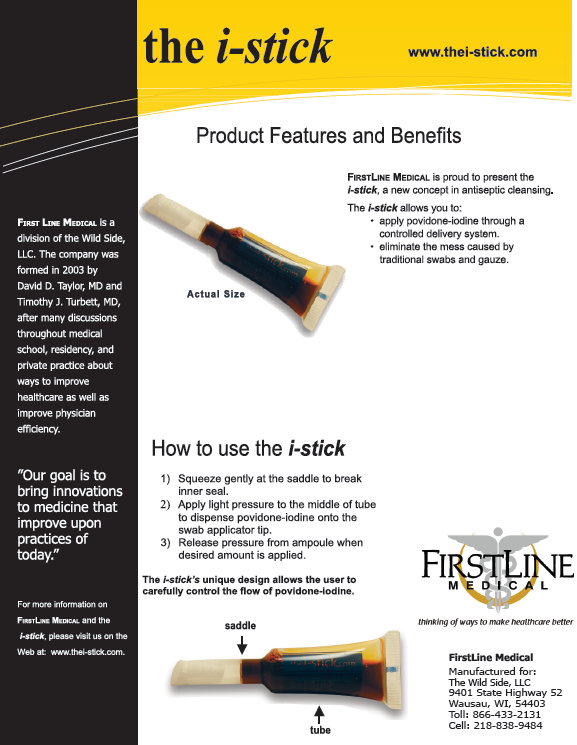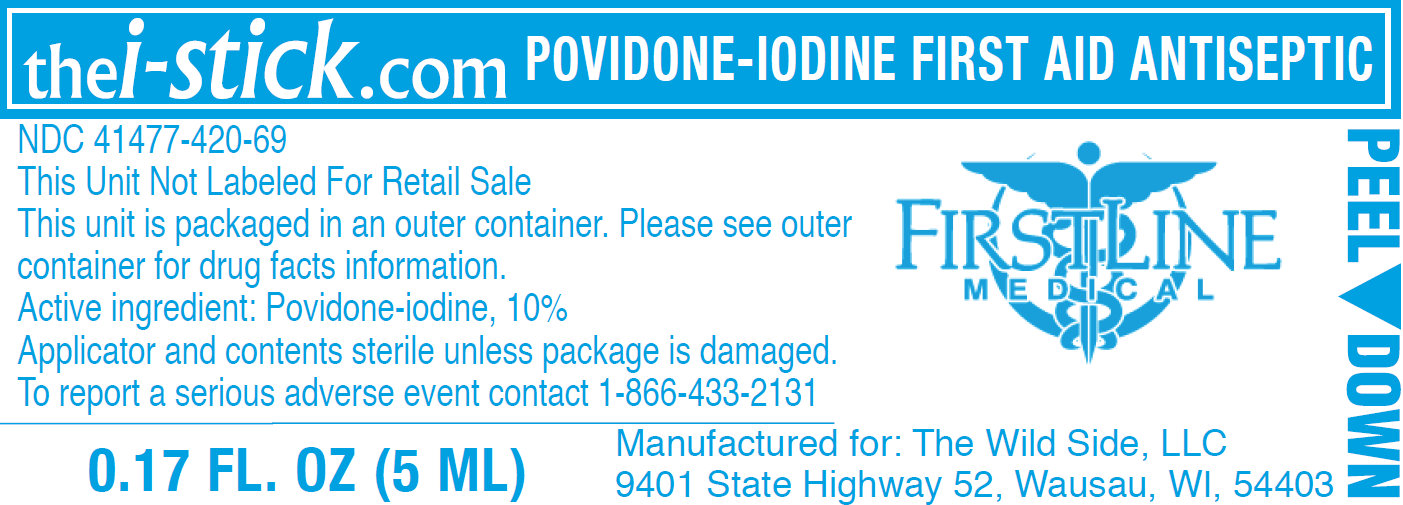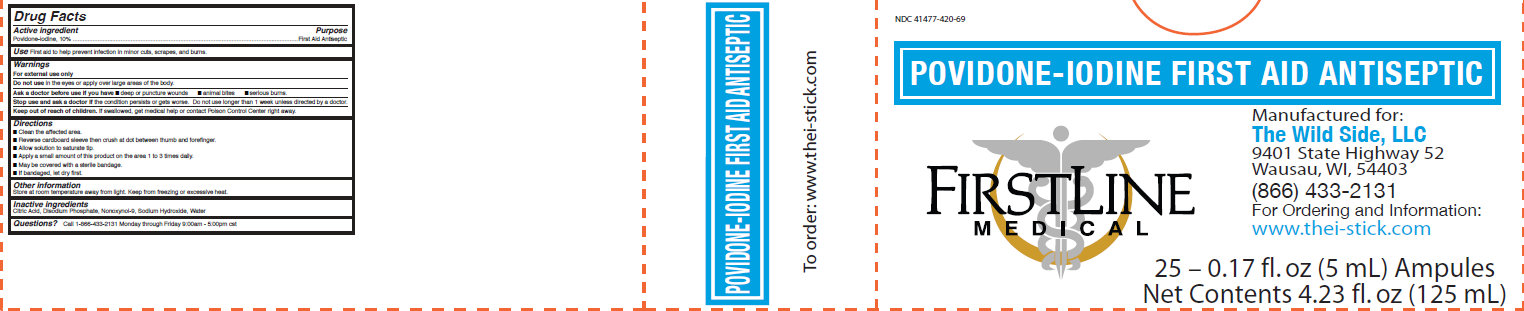 DRUG LABEL: FIRSTLINE MEDICAL the i-stick Povidone-Iodine Antiseptic Ampules
                
                
NDC: 41477-420 | Form: LIQUID
Manufacturer: The Wild Side, Llc dba Firstline Medical
Category: otc | Type: HUMAN OTC DRUG LABEL
Date: 20140115

ACTIVE INGREDIENTS: POVIDONE-IODINE 100 mg/1 mL
INACTIVE INGREDIENTS: CITRIC ACID MONOHYDRATE; SODIUM PHOSPHATE, DIBASIC, ANHYDROUS; NONOXYNOL-9; SODIUM HYDROXIDE; WATER

FIRSTLINE MEDICAL the i-stick Povidone-Iodine Antiseptic Ampules

Active ingredient

Povidone-iodine 10%

Purpose

Antiseptic

Uses

- Patient preoperative skin preparation
- For preparation of the skin prior to surgery
- Helps to reduce bacteria that potentially can cause skin infection

Warnings

For external use only.

Do not use

- in the eyes

When using this product

keep out of eyes, ears, and mouth

Stop use and ask a doctor if

- irritation and redness develop
- condition persists for more than 72 hours
- infection occurs

Keep out of reach of children.

- If swallowed, get medical help or contact a Poison Control Center right away.

Directions

- clean the area
- reverse cardboard sleeve then crush at dot between thumb and forefinger
- allow solution to saturate tip
- apply product to the operative site prior to surgery using the applicator tip

Other information

- Store at room temperature away from light
- Keep from freezing or excessive heat

Inactive ingredients

- citric acid, disodium phosphate, nonoxynol-9, sodium hydroxide, water

Questions?

call 1-866-433-2131 Monday through Friday 9:00am-5:00pm est

LINE MEDICAL the i-stick Povidone-Iodine Antiseptic Ampules 25 count (41477-420-69)

- Representative Package Labeling